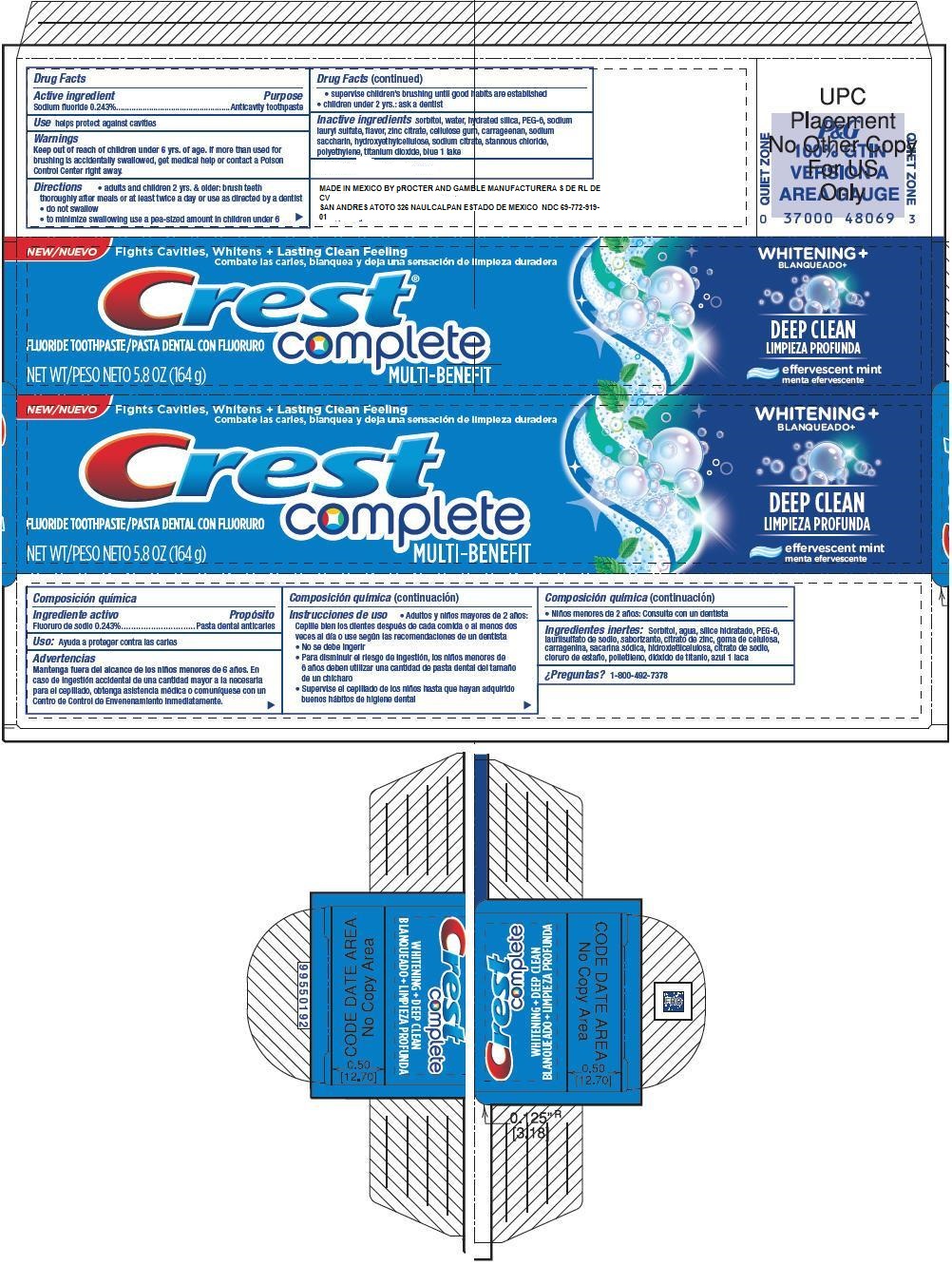 DRUG LABEL: Crest Complete Deep Clean
NDC: 69772-819 | Form: PASTE, DENTIFRICE
Manufacturer: Teresa Cecena DBA Genesis
Category: otc | Type: HUMAN OTC DRUG LABEL
Date: 20180629

ACTIVE INGREDIENTS: SODIUM FLUORIDE 2.43 mg/100 mL
INACTIVE INGREDIENTS: SORBITOL; WATER; HYDRATED SILICA; POLYETHYLENE GLYCOL 300; SODIUM LAURYL SULFATE; ZINC CITRATE; CARBOXYMETHYLCELLULOSE SODIUM; CARRAGEENAN; SACCHARIN SODIUM; STANNOUS CHLORIDE; SODIUM CITRATE; HIGH DENSITY POLYETHYLENE; TITANIUM DIOXIDE; FD&C BLUE NO. 1; ALUMINUM OXIDE

ACTIVE INGREDIENT

Sodium fluoride .243%

PURPOSE

Anticavity toothpaste

INDICATIONS AND USAGE

Help protect against cavities

KEEP OUT OF REACH OF CHILDREN

Keep out reach of children under 6 Yrs of age. If more than used fro brushong is accidentally swallowed get medical help or poison control center right away

DOSAGE AND ADMINISTRATION

Direccions

- adults and children 5 yrs and older: brush teeth thoroughly after meals or at least twice a day or use as directed by a dentist
- do not swallow
- to minimiza swallowing use a pea-sized amount in children under 63
- supervise children's brushing until good habits are established
- children under 2 years as a dentist

INACTIVE INGREDIENT

sorbitol,water,hydrated silica, PED-6, sodium lauryl sulfate, flavor,zinc citrate,cellulose gum,carrageenan, soium saccharin, hydroxyethlcellulose,sodium citrate, stannoum chloride,chloride,polyyethylene,titanium dioxide,blue 1 lake

Keep out of reach of children under 6 years